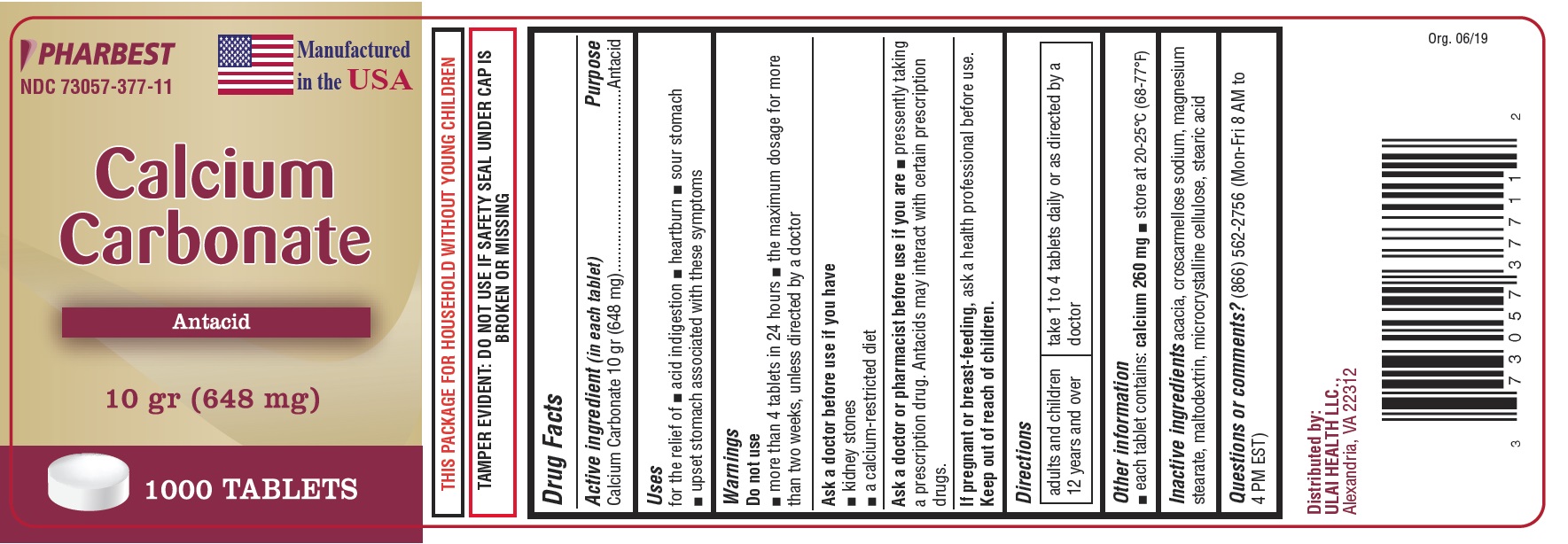 DRUG LABEL: Calcium Carbonate 10 gr (648 mg)
NDC: 73057-377 | Form: TABLET
Manufacturer: Ulai Health LLC
Category: otc | Type: HUMAN OTC DRUG LABEL
Date: 20250120

ACTIVE INGREDIENTS: CALCIUM CARBONATE 648 mg/1 1
INACTIVE INGREDIENTS: ACACIA; CROSCARMELLOSE SODIUM; MAGNESIUM STEARATE; MALTODEXTRIN; MICROCRYSTALLINE CELLULOSE; STEARIC ACID

Drug Facts

Active ingredient (in each tablet)

Calcium Carbonate 10 gr (648 mg)

Purpose

Antacid

Uses

for the relief of

- acid indigestion
- heartburn
- sour stomach
- upset stomach associated with these symptoms

Do not use

- more than 4 tablets in 24 hours
- the maximum dosage for more than two weeks, unless directed by a doctor

Ask a doctor before use if you have

- kidney stones
- a calcium-restricted diet

Ask a doctor or pharmacist before use if you are

- presently taking a prescription drug. Antacids may interact with certain prescription drugs.

If pregnant or breast-feeding,

ask a health professional before use.

Directions

adults and children 12 years and over | take 1 to 4 tablets daily or as directed by a doctor

Other information

- each tablet contains: calcium 260 mg
- store at 20-25oC (68-77oF)

Inactive ingredients

acacia, croscarmellose sodium, magnesium stearate, maltodextrin, microcrystalline cellulose, stearic acid

Questions or comments?

(866) 562-2756 (Mon- Fri 8 AM to 4 PM EST)

PACKAGE LABEL

PHARBEST

NDC 73057-377-11

Manufactured in the USA

Calcium

Carbonate

Antacid

10 gr (648 mg)

1000 TABLETS